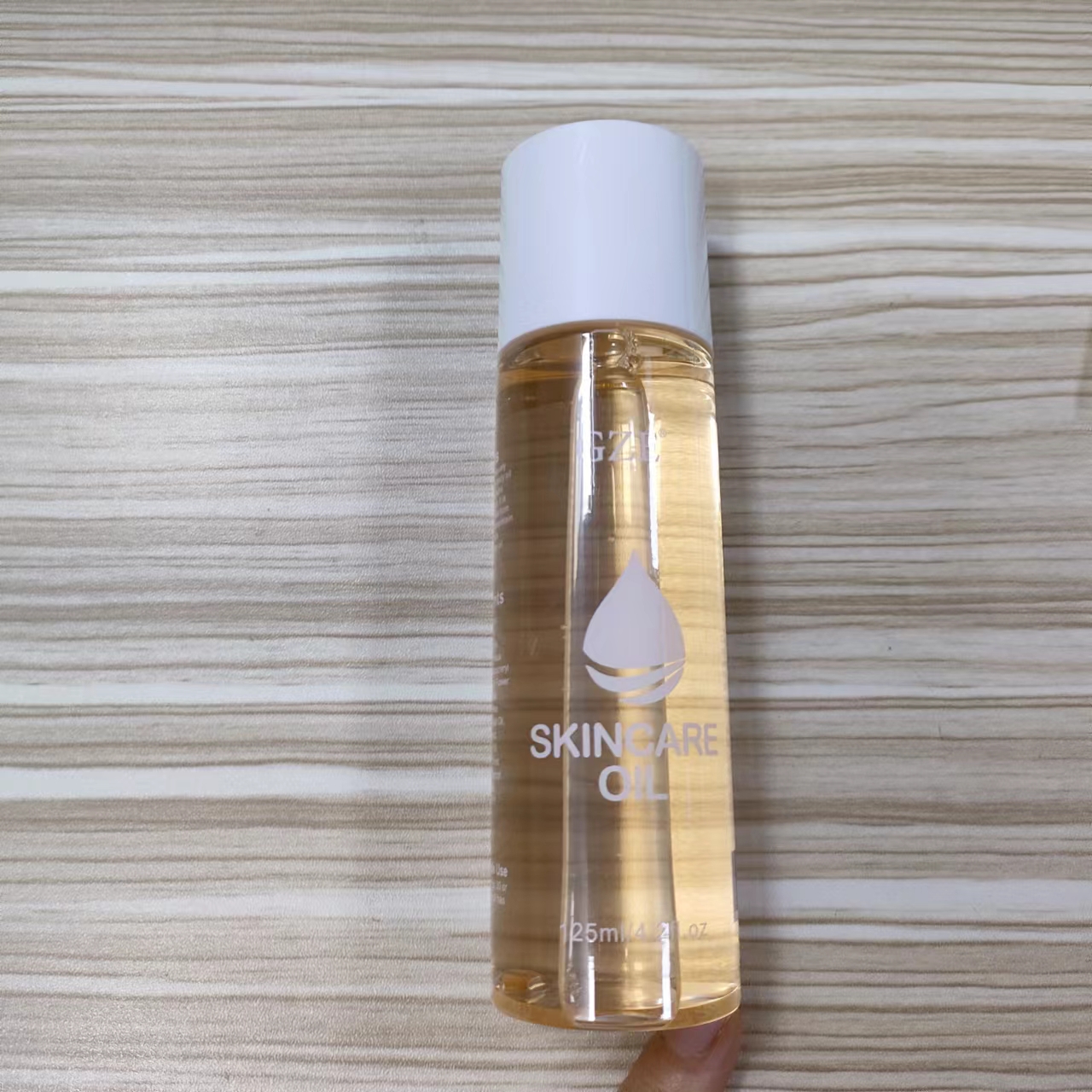 DRUG LABEL: GZE Skincare Oil
NDC: 74458-155 | Form: OIL
Manufacturer: Guangzhou Yilong Cosmetics Co., Ltd
Category: otc | Type: HUMAN OTC DRUG LABEL
Date: 20241129

ACTIVE INGREDIENTS: BISABOLOL 0.5 g/100 mL
INACTIVE INGREDIENTS: RETINYL PALMITATE; ANTHEMIS NOBILIS FLOWER OIL; GERANIOL; RED 17; CETEARYL ETHYLHEXANOATE; LAVANDULA ANGUSTIFOLIA (LAVENDER) OIL; ROSMARINUS OFFICINALIS (ROSEMARY) LEAF OIL; GLYCINE SOJA (SOYBEAN) OIL; EUGENOL; .ALPHA.-TOCOPHEROL ACETATE; MINERAL OIL; HELIANTHUS ANNUUS (SUNFLOWER) SEED OIL; TRIISONONANOIN; ISOPROPYL MYRISTATE; CALENDULA OFFICINALIS FLOWER

GZE SKINCARE OIL

ACTIVE INGREDIENT

Bisabolol 0.5%

INACTIVE INGREDIENT

Mineral Oil

Triisononanoin

Cetearyl Ethylhexanoate

Isopropyl Myristate

Retinyl Palmitate

Helianthus Annuus (Sunflower) Seed Oil

Tocopheryl Acetate

Anthemis Nobilis Flower Oil

Lavandula Angustifolia (Lavender) Oil

Rosmarinus Officinalis (Rosemary) Leaf Oil

Calendula Officinalis Extract

Glycine Soja (Soybean) Oil

Tocopherol/Wheat Polypeptides

Parfum

Benzyl Salitcylate

Polycitronellol

Eugenol

Geraniol

Red 17

PURPOSE

Moisturizing.

WARNINGS

For external use only.

Stop use and ask a doctor if rash occurs.

INDICATIONS AND USAGE

Massage into the skin for 30
ormore seconds until the oil has absorbed.

Do not use on damaged or broken skin.

When using this product keep out of eyes. Rinse with water to remove.

Keep out of reach of children. If swallowed, get medical help or contact a Poison Control Center right away.

DOSAGE AND ADMINISTRATION

Massage into the skin for 30
ormore seconds until the oil has absorbed.